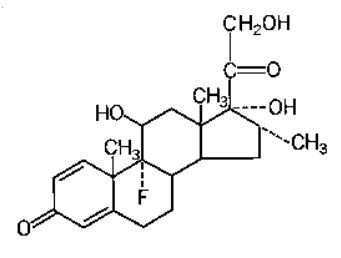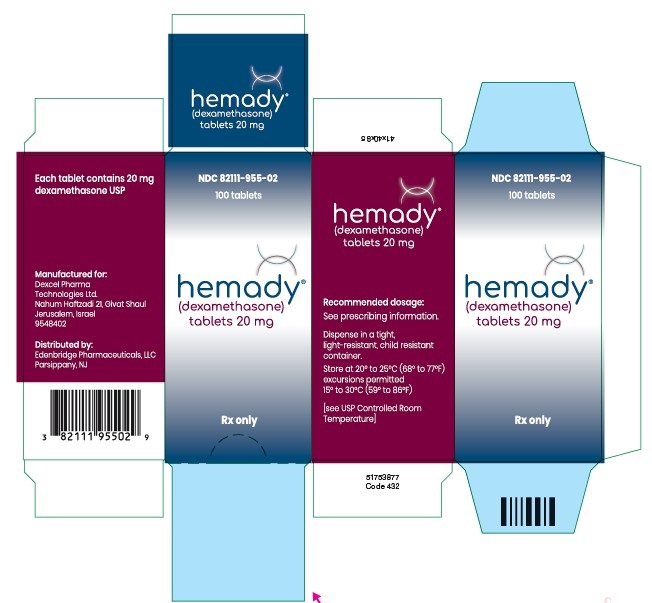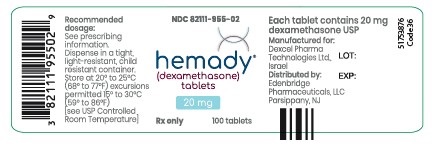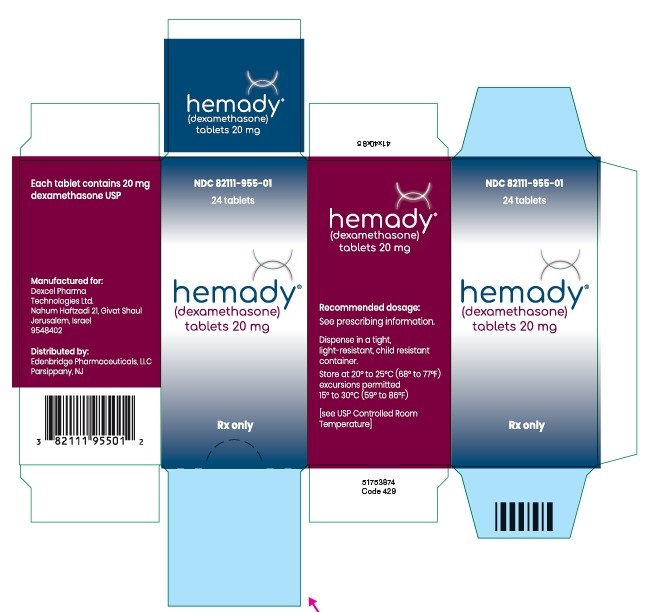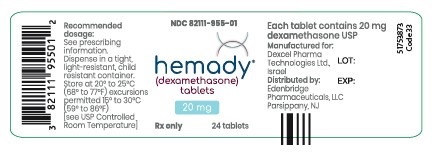 DRUG LABEL: Hemady
NDC: 82111-955 | Form: TABLET
Manufacturer: Edenbridge Pharmaceuticals LLC.
Category: prescription | Type: Human Prescription Drug Label
Date: 20260109

ACTIVE INGREDIENTS: DEXAMETHASONE 20 mg/1 1
INACTIVE INGREDIENTS: STARCH, CORN; LACTOSE MONOHYDRATE; MAGNESIUM STEARATE; POVIDONE K30; SODIUM STARCH GLYCOLATE TYPE A POTATO

HIGHLIGHTS OF PRESCRIBING INFORMATION

These highlights do not include all the information needed to use HEMADY® safely and effectively. See full prescribing information for HEMADY.
HEMADY (dexamethasone tablets), for oral use
Initial U.S. Approval: 1958

RECENT MAJOR CHANGES

Warnings and Precautions, Immunosuppression and Increased Risk of Infection (5.2) 6/2024

Warnings and Precautions, Kaposi’s Sarcoma (5.11) 6/2024

1 INDICATIONS AND USAGE

HEMADY is a corticosteroid indicated in combination with other anti-myeloma products for the treatment of adults with multiple myeloma. (‎1)

2 DOSAGE AND ADMINISTRATION

Recommended Dosage: 20 mg or 40 mg orally once daily, on specific days depending on the protocol regimen. (‎2)

3 DOSAGE FORMS AND STRENGTHS

Tablets: 20 mg (‎3)

4 CONTRAINDICATIONS

• Patients with hypersensitivity to dexamethasone (‎4)
• Patients with systemic fungal infections (‎4)

5 WARNINGS AND PRECAUTIONS

• Alterations in Endocrine Function: Hypothalamic-pituitary adrenal (HPA) axis suppression, Cushing’s syndrome, and hyperglycemia can occur. Monitor patients for these conditions with chronic use. (‎5.1)
• Immunosuppression and Increased Risk of Infections: Increased risk of new, exacerbation, dissemination, or reactivation of latent infections. (‎5.2)
• Alteration in Cardiovascular/Renal Function: Monitor for elevated blood pressure and sodium, and for decreased potassium levels. (‎5.3)
• Venous and Arterial Thromboembolism: Risk increased; consider anticoagulant prophylaxis and monitor for evidence of thromboembolism. (‎5.4)
• Vaccination: Avoid the administration of live or live attenuated vaccines in patients receiving immunosuppressive doses of corticosteroids. (‎5.5)
• Ophthalmic Effects: May include cataracts, infections, and glaucoma. (‎5.6)
• Gastrointestinal Perforation: Avoid use in active or latent peptic ulcers, diverticulitis, fresh intestinal anastomoses, and nonspecific ulcerative colitis, since they may increase the risk of a perforation. (‎5.7)
• Osteoporosis: Increased risk; monitor for changes in bone density with chronic use. (‎5.8)
• Behavioral and Mood Disturbances: May include euphoria, insomnia, mood swings, personality changes, severe depression, and psychosis. Monitor for signs and symptoms and manage promptly. (‎5.10)
• Kaposi’s Sarcoma: Kaposi’s sarcoma has been reported to occur in patients receiving corticosteroid therapy, most often for chronic conditions. (‎5.11)
• Embryo-Fetal Toxicity: Can cause fetal harm. Advise females of reproductive potential of the potential risk to a fetus. (‎5.13, ‎8.1)

6 ADVERSE REACTIONS

The most common adverse reactions are cardiovascular, dermatologic, endocrine, fluid and electrolyte disturbances, gastrointestinal, metabolic, musculoskeletal, neurological/psychiatric, ophthalmic, abnormal fat deposits, decreased resistance to infection, hiccups, increased or decreased motility and number of spermatozoa, malaise, moon face, and weight gain. (‎6)
To report SUSPECTED ADVERSE REACTIONS, contact Edenbridge Pharmaceuticals, LLC, at 877-381-3336 or FDA at 1-800-FDA-1088 or www.fda.gov/medwatch.

7 DRUG INTERACTIONS

• Avoid concomitant use of strong CYP3A4 inhibitors or inducers. (‎7.1)
• Concomitant therapies such as erythropoietin stimulating agents or estrogen containing therapies may have an increased risk of thromboembolism. (‎7.2)

8 USE IN SPECIFIC POPULATIONS

Lactation: Advise not to breastfeed. (‎8.2)

FULL PRESCRIBING INFORMATION

1 INDICATIONS AND USAGE

HEMADY is indicated in combination with other anti-myeloma products for the treatment of adults with multiple myeloma (MM).

2 DOSAGE AND ADMINISTRATION

2.1 Recommended Dosage

The recommended dosage of HEMADY is 20 mg or 40 mg, orally, once daily, on specific days depending on the treatment regimen. Refer to the Prescribing Information of the other anti-myeloma products used in combination with HEMADY for specific HEMADY dosing. HEMADY can be administered with or without food.

2.2 Dose Modification for Elderly Patients

Dose-reduction for HEMADY is recommended for elderly patients, due to increased toxicity in these patients. Refer to the Prescribing Information of the other anti-myeloma products used as part of a combination regimen with HEMADY, for dosing recommendations in elderly patients.

3 DOSAGE FORMS AND STRENGTHS

Tablets: 20 mg white, round, biconvex tablet embossed with “20” on one side.

4 CONTRAINDICATIONS

HEMADY is contraindicated in patients with:

- Hypersensitivity to dexamethasone, or any of the excipients. Rare instances of anaphylactic reactions have been reported [see Adverse Reactions (‎6), Description (‎11)].
- Systemic fungal infections. Corticosteroids may exacerbate systemic fungal infections [see Warnings and Precautions (‎5.2)].

5 WARNINGS AND PRECAUTIONS

5.1 Alterations in Endocrine Function

Corticosteroids, such as HEMADY, can cause serious and life-threatening alterations in endocrine function, especially with chronic use. Monitor patients receiving HEMADY for adrenal insufficiency after corticosteroid withdrawal and Cushing’s syndrome and hyperglycemia while receiving corticosteroids. In addition, patients with hypopituitarism, primary adrenal insufficiency, or congenital adrenal hyperplasia, altered thyroid function, or pheochromocytoma may be at risk for adverse endocrine events.

Risk of Adrenal Insufficiency Following Corticosteroid Withdrawal

Corticosteroids can produce reversible hypothalamic-pituitary adrenal (HPA) axis suppression, with the potential for the development of secondary adrenal insufficiency after withdrawal of corticosteroid treatment. Acute adrenal insufficiency can occur if glucocorticoids are withdrawn abruptly and can be fatal. The degree and duration of adrenocortical insufficiently produced is variable among patients and depends on the dose, frequency, and duration of glucocorticoid therapy. The risk may be reduced by gradually tapering the corticosteroid dose when withdrawing treatment. This insufficiency may persist for months after discontinuation of therapy; therefore, in any situation of stress occurring during that period, corticosteroid therapy should be reinstituted. For patients already taking corticosteroids during times of stress, the dosage may have to be increased.

A steroid “withdrawal syndrome”, seemingly unrelated to adrenocortical insufficiency, may also occur following abrupt discontinuance of corticosteroids. This syndrome includes symptoms such as: anorexia, nausea, vomiting, lethargy, headache, fever, joint pain, desquamation, myalgia, and/or weight loss. These effects are thought to be due to the sudden change in glucocorticoid concentration rather than to low corticosteroid levels.

Cushing’s Syndrome

Cushing’s syndrome (hypercortisolism) may occur with prolonged exposure to exogenous corticosteroids, including HEMADY. Symptoms include hypertension, truncal obesity and thinning of the limbs, purple striae, facial rounding, facial plethora, muscle weakness, easy and frequent bruising with thin fragile skin, posterior neck fat deposition, osteopenia, acne, amenorrhea, hirsutism and psychiatric abnormalities. Using the lowest dose of corticosteroid for the shortest duration possible may reduce the risk.

Hyperglycemia

Corticosteroids can increase blood glucose, worsen pre-existing diabetes, and predispose those on long-term therapy to diabetes mellitus, and may reduce the effect of the antidiabetic drugs. Monitor blood glucose at regular intervals. For patients with hyperglycemia, anti-diabetic treatment should be initiated or adjusted accordingly.

Considerations for Use in Patients with Altered Thyroid Function

Metabolic clearance of corticosteroids is decreased in hypothyroid patients and increased in hyperthyroid patients. Changes in thyroid status of the patient may necessitate a dose adjustment of the corticosteroid. When concomitant administration of corticosteroids and levothyroxine is required, administration of corticosteroid should precede the initiation of levothyroxine therapy to avoid adrenal crisis.

Pheochromocytoma Crisis

There have been reports of pheochromocytoma crisis, which can be fatal, after administration of systemic corticosteroids. In patients with suspected or identified pheochromocytoma, consider the risk of pheochromocytoma crisis prior to administering HEMADY.

5.2 Immunosuppression and Increased Risk of Infection

Corticosteroids, including HEMADY, suppress the immune system and increase the risk of infection with any pathogen, including viral, bacterial, fungal, protozoan, or helminthic pathogens. Corticosteroids can:

- Reduce resistance to new infections
- Exacerbate existing infections
- Increase the risk of disseminated infections
- Increase the risk of reactivation or exacerbation of latent infections
- Mask some signs of infection

Corticosteroid-associated infections can be mild but can be severe and at times fatal. The rate of infectious complications increases with increasing corticosteroid dosages.
Monitor for the development of infection and consider HEMADY withdrawal or dosage reduction as needed.

Tuberculosis

If HEMADY is used to treat a condition in patients with latent tuberculosis or tuberculin reactivity, reactivation of tuberculosis may occur. Closely monitor such patients for reactivation. During prolonged HEMADY therapy, patients with latent tuberculosis or tuberculin reactivity should receive chemoprophylaxis.
Varicella Zoster and Measles Viral Infections
Varicella and measles can have a serious or even fatal course in non-immune pediatric and adult patients taking corticosteroids, including HEMADY. In corticosteroid-treated patients who have not had these diseases or are non-immune, particular care should be taken to avoid exposure to varicella and measles:

- If a HEMADY-treated patient is exposed to varicella, prophylaxis with varicella zoster immune globulin may be indicated. If varicella develops, treatment with antiviral agents may be considered.
- If a HEMADY-treated patient is exposed to measles, prophylaxis with immunoglobulin may be indicated.

Hepatitis B Virus Reactivation
Hepatitis B virus reactivation can occur in patients who are hepatitis B carriers treated with immunosuppressive dosages of corticosteroids, including HEMADY. Reactivation can also occur infrequently in corticosteroid-treated patients who appear to have resolved hepatitis B infection.
Screen patients for hepatitis B infection before initiating immunosuppressive (e.g., prolonged) treatment with HEMADY. For patients who show evidence of hepatitis B infection, recommend consultation with physicians with expertise in managing hepatitis B regarding monitoring and consideration for hepatitis B antiviral therapy.
Fungal Infections
Corticosteroids, including HEMADY, may exacerbate systemic fungal infections; therefore, avoid HEMADY use in the presence of such infections unless HEMADY is needed to control drug reactions. For patients on chronic HEMADY therapy who develop systemic fungal infections, HEMADY withdrawal or dosage reduction is recommended.
Amebiasis
Corticosteroids, including HEMADY, may activate latent amebiasis. Therefore, it is recommended that latent amebiasis or active amebiasis be ruled out before initiating HEMADY in patients who have spent time in the tropics or patients with unexplained diarrhea.
Strongyloides Infestation

Corticosteroids, including HEMADY, should be used with great care in patients with known or suspected Strongyloides (threadworm) infestation. In such patients, corticosteroid-induced immunosuppression may lead to Strongyloides hyperinfection and dissemination with widespread larval migration, often accompanied by severe enterocolitis and potentially fatal gram-negative septicemia.
Cerebral Malaria
Avoid corticosteroids, including HEMADY, in patients with cerebral malaria.

5.3 Alterations in Cardiovascular/Renal Function

Corticosteroids, including HEMADY, can cause elevation of blood pressure, salt, and water retention, and increased excretion of potassium and calcium. Monitor blood pressure and assess for signs and symptoms of volume overload. Monitor serum potassium levels. Dietary salt restriction and potassium supplementation may be necessary. HEMADY should be used with caution in patients with congestive heart failure.

Literature reports suggest an association between use of corticosteroids and left ventricular free wall rupture after a recent myocardial infarction; therefore, therapy with HEMADY should be used with great caution in these patients.

5.4 Venous and Arterial Thromboembolism

Thromboembolism is a known adverse reaction of dexamethasone, including HEMADY. The risk for venous and arterial thromboembolism increases significantly when dexamethasone is administered with anti-myeloma products (e.g., thalidomide, lenalidomide, pomalidomide, and carfilzomib). Refer to the Prescribing Information of these anti-myeloma products for information about the risk of venous and arterial thromboembolism.

Consider thromboprophylaxis based on an assessment of individual patients’ underlying risk factors and the anti-myeloma drugs. Agents that also may increase the risk of thromboembolism should be used with caution in patients with multiple myeloma receiving combination regimens of HEMADY and anti-myeloma products.

5.5 Vaccination

Avoid administration of live or live attenuated vaccines in patients receiving immunosuppressive doses of corticosteroids for the treatment of multiple myeloma. Killed or inactivated vaccines may be administered. However, the response to such vaccines cannot be predicted.

5.6 Ophthalmic Effects

Use of corticosteroids may produce posterior subcapsular cataracts, glaucoma with possible damage to the optic nerves, and may enhance the establishment of secondary ocular infections due to bacteria, fungi, or viruses.

Consider referral to an ophthalmologist for patients who develop ocular symptoms or use corticosteroid-containing products for more than 6 weeks. The use of oral corticosteroids is not recommended in the treatment of optic neuritis and may lead to an increase in the risk of new episodes.

Corticosteroids should not be used in patients with active ocular herpes simplex.

Intraocular pressure may become elevated in some individuals. If steroid therapy is continued for more than 6 weeks, intraocular pressure should be monitored.

5.7 Gastrointestinal Perforation

There is an increased risk of gastrointestinal perforation during corticosteroid use in patients with certain gastrointestinal disorders such as active or latent peptic ulcers, diverticulitis, fresh intestinal anastomoses, and nonspecific ulcerative colitis.

Signs of gastrointestinal perforation, such as peritoneal irritation, may be masked in patients receiving corticosteroids. Avoid corticosteroids if there is a possibility of impending perforation, abscess, or other pyrogenic infections; diverticulitis; fresh intestinal anastomoses; or active or latent peptic ulcer.

5.8 Osteoporosis

Corticosteroids decrease bone formation and increase bone resorption both through their effect on calcium regulation (i.e., decreasing absorption and increasing excretion) and inhibition of osteoblast function. This, together with a decrease in the protein matrix of the bone, secondary to an increase in protein catabolism, and reduced sex hormone production, may lead to inhibition of bone growth in pediatric patients and the development of osteoporosis at any age. Special consideration should be given to patients at increased risk of osteoporosis (e.g., postmenopausal women) before initiating HEMADY therapy.

5.9 Myopathy

An acute myopathy has been observed with the use of high doses of corticosteroids, most often occurring in patients with disorders of neuromuscular transmission (e.g., myasthenia gravis), or in patients receiving concomitant therapy with neuromuscular blocking drugs (e.g., pancuronium). This acute myopathy is generalized, may involve ocular and respiratory muscles, and may result in quadriparesis. Elevation of creatine kinase may occur. Clinical improvement or recovery after stopping corticosteroids may require weeks to years.

5.10 Behavioral and Mood Disturbances

Potentially severe psychiatric adverse reactions may occur with systemic corticosteroids, including HEMADY. Symptoms typically emerge within a few days or weeks of starting treatment and may be dose-related. These reactions may improve after either dose reduction or withdrawal, although pharmacologic treatment may be necessary. Psychiatric adverse reactions usually involve hypomanic or manic symptoms (e.g., euphoria, insomnia, mood swings) during treatment and depressive episodes after discontinuation of treatment. Inform patients and caregivers of the potential for behavioral and mood changes and encourage them to seek medical attention if psychiatric symptoms develop, especially if depressed mood or suicidal ideation is suspected.

5.11 Kaposi's Sarcoma

Kaposi’s sarcoma has been reported to occur in patients receiving corticosteroid therapy, most often for chronic conditions. Discontinuation of corticosteroids may result in clinical improvement of Kaposi’s sarcoma.

5.12 HEMADY in Combination with Anti-Myeloma Products

HEMADY is administered in combination regimens with anti-myeloma products; please refer to the Prescribing Information of these products for additional information.

5.13 Embryo-Fetal Toxicity

Based on findings from clinical and animal reproduction studies, corticosteroids, including HEMADY, can cause fetal harm when administered to a pregnant woman. Dexamethasone administration to pregnant women has resulted in adverse effects on fetal growth, skeletal development/osteogenesis and low birth weight with prolonged use. Dexamethasone administration to pregnant animals during organogenesis resulted in structural abnormalities, embryo-fetal mortality, functional impairment, and alterations to growth at doses equivalent to or below the recommended doses.

Advise pregnant women of the potential risk to a fetus. Advise females of reproductive potential to use effective contraception during treatment with HEMADY and for at least one month after the last dose [see Use in Specific Populations (‎8.1, ‎8.3)].

6 ADVERSE REACTIONS

The following clinically significant adverse reactions are described in detail in other labeling sections:

- Hypersensitivity [see Contraindications (‎4)]
- Alterations in Endocrine Function [see Warnings and Precautions (‎5.1)]
- Immunosuppression and Increased Risk of Infections [see Warnings and Precautions (‎5.2)]
- Alterations in Cardiovascular/Renal Function [see Warnings and Precautions (‎5.3)]
- Venous and Arterial Thromboembolism [see Warnings and Precautions (‎5.4)]
- Vaccination [see Warnings and Precautions (‎5.5)]
- Ophthalmic Effects [see Warnings and Precautions (‎5.6)]
- Gastrointestinal Perforation [see Warnings and Precautions (‎5.7)]
- Osteoporosis [see Warnings and Precautions (‎5.8)]
- Myopathy [see Warnings and Precautions (‎5.9)]
- Behavioral and Mood Disturbances [see Warnings and Precautions (‎5.10)]
- Kaposi's Sarcoma [see Warnings and Precautions (‎5.11)]
- HEMADY in Combination with Anti-Myeloma Products [see Warnings and Precautions (‎5.12)]
- Embryo-Fetal Toxicity [see Warnings and Precautions (‎5.13)]

The following adverse reactions associated with the use of HEMADY or other corticosteroids were identified in clinical trials or postmarketing reports. Because these reactions were reported voluntarily from a population of uncertain size, it is not always possible to estimate their frequency reliably or to establish a causal relationship to drug exposure.
Allergic reactions: Allergic or hypersensitivity reaction, anaphylaxis, angioedema.
Blood and Lymphatic System Disorders: Leukocytosis.
Cardiovascular: Bradycardia, cardiac arrest, cardiac arrhythmias, cardiac enlargement, circulatory collapse, congestive heart failure, fat embolism, hypertension, hypertrophic cardiomyopathy in premature infants, myocardial rupture following recent myocardial infarction, edema, pulmonary edema, syncope, tachycardia, thromboembolism, thrombophlebitis, vasculitis.
Dermatologic: Acne, allergic dermatitis, cutaneous and subcutaneous atrophy, dry scaly skin, ecchymoses and petechiae, edema, erythema, hyperpigmentation, hypopigmentation, impaired wound healing, increased sweating, sterile abscess, rash, striae, suppressed reactions to skin tests, thin fragile skin, thinning scalp hair, urticaria.
Endocrine: Decreased carbohydrate and glucose tolerance, development of cushingoid state, hyperglycemia, glycosuria, hirsutism, hypertrichosis, increased requirements for insulin or oral hypoglycemic agents in diabetes, manifestations of latent diabetes mellitus, menstrual irregularities, secondary adrenocortical and pituitary unresponsiveness (particularly in times of stress, as in trauma, surgery, or illness), suppression of growth in pediatric patients.
Fluid and electrolyte disturbances: Fluid retention, hypokalemic alkalosis, potassium loss, sodium retention, increased urinary excretion of calcium, tumor lysis syndrome.
Gastrointestinal: Abdominal distention, elevation in serum liver enzyme levels (usually reversible upon discontinuation), hepatomegaly, increased appetite, nausea, pancreatitis, peptic ulcer with possible perforation and hemorrhage, perforation of the small and large intestine (particularly in patients with inflammatory bowel disease), ulcerative esophagitis.
Infection: Decreased resistance to infection, injection site infections following non-sterile administration.
Metabolic: Negative nitrogen balance due to protein catabolism.
Musculoskeletal: Osteonecrosis of femoral and humeral heads, Charcot-like arthropathy, loss of muscle mass, muscle weakness, osteoporosis, pathologic fracture of long bones, steroid myopathy, tendon rupture, vertebral compression fractures.
Neurological: Convulsions, epidural lipomatosis, headache, increased intracranial pressure with papilledema (pseudotumor cerebri) usually following discontinuation of treatment, neuritis, neuropathy, paresthesia, vertigo.
Ophthalmic: Central serous chorioretinopathy, exophthalmos, glaucoma, increased intraocular pressure, posterior subcapsular cataracts, vision blurred.
Other: Abnormal fat deposits, decreased resistance to infection, hiccups, increased or decreased motility and number of spermatozoa, malaise, moon face, weight gain.
Psychiatric: Depression, emotional instability, euphoria, insomnia, mood swings, personality changes, psychosis.
Reproductive: Alteration in motility and number of spermatozoa.

7 DRUG INTERACTIONS

7.1 Effect of Other Drugs on HEMADY

Strong CYP3A4 inhibitors
Coadministration of strong and moderate CYP3A4 inhibitors increased dexamethasone exposure [see Clinical Pharmacology (‎12.3)], which may increase the risk of adverse reactions [see Warnings and Precautions (‎5) and Adverse Reactions (‎6)]. Avoid coadministration of strong CYP3A4 inhibitors or consider alternative medication that are not strong CYP3A4 inhibitors. If concomitant use of strong CYP3A4 inhibitors cannot be avoided, closely monitor for adverse drug reactions.

Strong CYP3A4 inducers
Coadministration of strong CYP3A4 inducers may decrease dexamethasone exposure [see Clinical Pharmacology (‎12.3)], which may result in loss of efficacy. Avoid coadministration of strong CYP3A4 inducers or consider alternative medication that are not CYP3A4 inducers. If concomitant use strong CYP3A4 inducers cannot be avoided, consider increasing the dose of HEMADY.

Cholestyramine
Cholestyramine may increase the clearance of corticosteroids and potentially decrease corticosteroid exposure. Avoid coadministration of cholestyramine and HEMADY and consider alternative agents.

Anticholinesterases
Concomitant use of anticholinesterase agents and corticosteroids may produce severe weakness in patients with myasthenia gravis. If possible, anticholinesterase agents should be withdrawn at least 24 hours before initiating corticosteroid therapy.

Ephedrine
Ephedrine may decrease dexamethasone exposure. Decreased exposure may result in loss of efficacy. Consider increasing the dose of HEMADY when used concomitantly with ephedrine.

Estrogens, Including Oral Contraceptives
Estrogens may decrease the hepatic metabolism of certain corticosteroids and increase exposures, which may increase the risk of adverse reactions [see Warnings and Precautions (‎5) and Adverse Reactions (‎6)].

7.2 Effect of HEMADY on Other Drugs

CYP3A4 Substrates
Coadministration of dexamethasone with drugs that are CYP3A4 substrates may decrease the concentration of these drugs. This may result in loss of efficacy of these drugs.

Oral Anticoagulants
Coadministration of anticoagulants with corticosteroids may reduce the response to anticoagulants [see Adverse Reactions (‎6)]. Frequently monitor coagulation indices to maintain the desired anticoagulant effect when administered with HEMADY.

Amphotericin B Injection and Potassium-Depleting Agents
Sodium retention with resultant edema and potassium loss may occur in patients receiving corticosteroids [see Warnings and Precautions (‎5.3), and Adverse Reactions (‎6)]. Closely monitor potassium levels when potassium-depleting agents are coadministered with HEMADY. In addition, there have been cases reported in which concomitant use of amphotericin B and hydrocortisone was followed by cardiac enlargement and congestive heart failure.

Antidiabetics
Corticosteroids, including HEMADY, may increase blood glucose concentrations [see Warnings and Precautions (‎5.1) and Adverse Reactions (‎6)]. Consider adjusting the dose of antidiabetic agents, as necessary, when coadministered with HEMADY.

Isoniazid
Serum concentrations of isoniazid may be decreased with corticosteroids.

Cyclosporine
Increased activity of both cyclosporine and corticosteroids may occur when the two are used concurrently. Convulsions have been reported with this concurrent use.

Digitalis Glycosides
Patients on digitalis glycosides may be at increased risk of arrhythmias due to hypokalemia [see Warnings and Precautions (‎5.3) and Adverse Reactions (‎6)].

Nonsteroidal Anti-Inflammatory Agents (NSAIDS)
Concomitant use of aspirin (or other nonsteroidal anti-inflammatory agents) and corticosteroids increases the risk of gastrointestinal side effects [see Warnings and Precautions (‎5.7) and Adverse Reactions (‎6)]. The clearance of salicylates may be increased with concurrent use of corticosteroids. Monitor for toxicity when aspirin is used in conjunction with HEMADY in hypoprothrombinemia.

Phenytoin
In post-marketing experience, there have been reports of both increases and decreases in phenytoin levels with dexamethasone coadministration, leading to alterations in seizure control.

Vaccines
Patients on corticosteroid therapy may exhibit a diminished response to toxoids and live or inactivated vaccines due to inhibition of antibody response. Corticosteroids may also potentiate the replication of some organisms contained in live attenuated vaccines. If possible, defer routine administration of vaccines or toxoids until HEMADY therapy is discontinued [see Warnings and Precautions (‎5.5)].

Concomitant Therapies that May Increase the Risk of Thromboembolism
Erythropoietic agents, or other agents that may increase the risk of thromboembolism, such as estrogen containing therapies, coadministered with HEMADY may increase the risk of thromboembolism. Monitor for risk of thromboembolism in patients with MM receiving anti-myeloma products with HEMADY [see Warnings and Precautions (‎5.4)].

Thalidomide
Toxic epidermal necrolysis has been reported with concomitant use of thalidomide. Closely monitor for toxicity when thalidomide is coadministered with HEMADY.

7.3 Laboratory Test Interference

Skin Tests

Corticosteroids may suppress reactions to skin tests.

8 USE IN SPECIFIC POPULATIONS

8.1 Pregnancy

Risk Summary

Corticosteroids, including HEMADY, readily cross the placenta. Adverse developmental outcomes including orofacial clefts (cleft lip with or without cleft palate), intrauterine growth restriction, and decreased birth weight have been reported with maternal use of corticosteroids, including HEMADY, during pregnancy. In animal developmental and reproductive toxicology studies administration of corticosteroids to pregnant animals during organogenesis resulted in structural abnormalities, embryo-fetal mortality, functional impairment, and alterations to growth at doses equivalent to or below the recommended doses (see Data).

Advise pregnant women of the potential risk to a fetus.

HEMADY is administered in combination with anti-myeloma products that can cause embryo-fetal harm and are contraindicated for use in pregnancy. Refer to the Prescribing Information of the other anti-myeloma products used in combination with HEMADY for additional information.

The estimated background risk of major birth defects and miscarriage for the indicated population is unknown. All pregnancies have a background risk of birth defect, loss, or other adverse outcomes. The background risk in the U.S. general population of major birth defects is 2% to 4% and of miscarriage is 15% to 20% of clinically recognized pregnancies.

Data

Human Data

HEMADY should be used during pregnancy only if the potential benefit justifies the potential risk to the fetus. Multiple courses of antenatal dexamethasone had been associated with reduced birth weight, susceptibility to infections, and increase blood glucose level in the newborns. Neonatal hypoglycemia was also reported. Infants born to mothers who have received substantial doses of corticosteroids during pregnancy should be carefully observed for signs of hypoadrenalism.

Animal Data

In pregnant animals administered dexamethasone during organogenesis, doses equivalent to or below the recommended human dose have caused adverse developmental outcomes including structural abnormalities (cleft palate), alterations to growth (growth restrictions including reduced bone lengths and fetal weights), functional impairment (neurodevelopmental and metabolic effects), and embryo-fetal mortality (reduced number of embryonic implantations and fewer live fetuses).

8.2 Lactation

Risk Summary

Systemically administered corticosteroids appear in human milk and could suppress growth, interfere with endogenous corticosteroid production, or cause other untoward effects. Advise women not to breastfeed during treatment and for 2 weeks after the last dose.

8.3 Females and Males of Reproductive Potential

Pregnancy Testing
Pregnancy testing is recommended for females of reproductive potential prior to initiating HEMADY [see Use in Specific Populations (‎8.1)].
HEMADY is used in combination with other anti-myeloma products that require pregnancy testing in females of reproductive potential. Refer to the Prescribing Information for the products used in combination with HEMADY.

Contraception
Advise patients of reproductive potential to use effective contraception during treatment with HEMADY and for at least one month following the final dose of HEMADY.
HEMADY is used in combination with other anti-myeloma products that require contraception in females and males of reproductive potential. Refer to the Prescribing Information for the products used in combination with HEMADY.

Infertility
Males
Steroids may increase or decrease motility and number of spermatozoa in some patients. In animals, dexamethasone affects male spermatogenesis [see Nonclinical Toxicology (‎13.1)].

8.4 Pediatric Use

Safety and effectiveness in pediatric patients have not been established.

8.5 Geriatric Use

No overall differences in safety or effectiveness were observed between elderly subjects and younger subjects, and other reported clinical experience with dexamethasone has not identified differences in responses between the elderly and younger patients. However, the incidence of corticosteroid-induced adverse reactions may be increased in geriatric patients and are dose-related.
Osteoporosis is the most frequently encountered complication, which occurs at a higher incidence rate in corticosteroid-treated geriatric patients as compared to younger populations and in age-matched controls. Losses of bone mineral density appear to be greatest early on in the course of treatment and may recover over time after steroid withdrawal or use of lower doses. Higher doses increase the relative risk of both vertebral and nonvertebral fractures, even in the presence of higher bone density compared to patients with involution osteoporosis. Perform routine screening of geriatric patients, including regular assessments of bone mineral density and institution of fracture prevention strategies, along with regular review of the dose of and need for continued dexamethasone therapy [see Warnings and Precautions (‎5.8)].
HEMADY is used in combination with other anti-myeloma products. Refer to the Prescribing Information of the other anti-myeloma products used as part of a combination regimen with HEMADY, for information on the use of those products in elderly patients.

10 OVERDOSAGE

Treatment of overdosage is by supportive and symptomatic therapy. In the case of acute overdosage, according to the patient’s condition, supportive therapy may include gastric lavage or induced vomiting.

11 DESCRIPTION

HEMADY (dexamethasone, USP) is an anti-inflammatory, 9-fluoro-glucocorticoid. The chemical name is 9-fluoro-11β,17,21trihydroxy-16α-methylpregna-1,4-diene-3,20-dione. The molecular weight is 392.47 g/mol. The molecular formula is C22H29FO5. The structural formula is:

Dexamethasone is a white to practically white, odorless, crystalline powder. It is stable in air. It is practically insoluble in water.

HEMADY for oral administration is available as an immediate-release tablet in a strength of 20 mg. Each tablet contains dexamethasone USP and the following inactive ingredients: corn starch NF, lactose monohydrate NF, magnesium stearate NF, povidone NF, and sodium starch glycolate NF.

12 CLINICAL PHARMACOLOGY

12.1 Mechanism of Action

Dexamethasone is a corticosteroid with anti-inflammatory effects and low mineralocorticoid activity. The precise mechanism of action in multiple myeloma is unknown. Dexamethasone induces apoptosis of multiple myeloma cells.

12.2 Pharmacodynamics

Following oral administration of a single dose of dexamethasone tablet to healthy subjects, the decrease in mean baseline cortisol concentration was maximal by 12 hours post-dose, with mean cortisol concentrations returning to near baseline approximately 3 days after drug administration.

12.3 Pharmacokinetics

The pharmacokinetics of oral dexamethasone were dose proportional between single dose of 0.5 to 40 mg. Following a single HEMADY dose of 20 mg, the geometric mean (coefficient of variation, %CV) dexamethasone peak concentrations (Cmax) was 247 ng/mL (31%) and area under the curve over time to infinity (AUCinf) was 1271 ng.hr/mL (31%) in subjects.

Absorption

Following 20 mg dose of HEMADY, dexamethasone median time to peak concentrations (Tmax) was 1 hour (range: 0.5 to 4 hours).

Effect of Food

A high-fat, high-calorie (total 800-1000 calories: approximately 60% from fat, 25% from carbohydrate and 15% from protein) meal had no effect on AUCinf and decreased Cmax by 23% of a single 20 mg dose of HEMADY.

Distribution

Dexamethasone is about 77% bound to human plasma proteins in vitro.

Elimination

The mean terminal half-life (coefficient of variation) of dexamethasone is 4 hours (18%) and oral clearance (CL/F) was 15.7 L/hr following a single dose of HEMADY.

Metabolism

Dexamethasone is metabolized by CYP3A4.

Excretion

Renal excretion of dexamethasone is less than 10% of total body clearance. Less than 10% of dexamethasone is excreted in the urine.

Specific Populations

The effect of baseline renal and hepatic impairment on the pharmacokinetics of dexamethasone has not been studied.

Drug Interactions Studies

Effect of Strong and Moderate CYP3A4 Inhibitors

Coadministration of itraconazole (strong CYP3A4 inhibitor: 200 mg once daily x 4 days) with a single dose of oral dexamethasone (4.5 mg) increased dexamethasone AUCinf by 3.7-fold [see Drug Interactions (‎7.1)].

Coadministration of aprepitant (moderate CYP3A4 inhibitor: 125 mg on Day 1, and 80 mg once daily on Days 2 to 5) with oral dexamethasone (20 mg on Day 1, and 8 mg once daily on Day 2-5) increased dexamethasone AUCinf by 2.2 -fold on Day 1 and 5 [see Drug Interactions (‎7.1)].

Effects of Other Anti-Myeloma Products

Coadministration of thalidomide, lenalidomide, pomalidomide, ixazomib, bortezomib or carfilzomib with dexamethasone is not expected to affect the pharmacokinetics of dexamethasone.

Effect on Other Anti-Myeloma Products

Coadministration of dexamethasone had no effect on the mean AUCinf of lenalidomide, pomalidomide, ixazomib, and bortezomib.

Coadministration of dexamethasone with carfilzomib or thalidomide is not expected to affect the pharmacokinetics of these drugs, as these drugs are not primarily metabolized by CYP3A4 in vitro.

For additional information on the drug interaction studies with dexamethasone and other anti-myeloma products, refer to the Prescribing Information of the other anti-myeloma products.

13 NONCLINICAL TOXICOLOGY

13.1 Carcinogenesis, Mutagenesis, Impairment of Fertility

No adequate studies have been conducted in animals to determine whether corticosteroids have a potential for carcinogenesis.

Dexamethasone was tested for in vitro and in vivo genotoxic potential and was positive in the following assays: chromosomal aberrations and sister-chromatid exchanges in human lymphocytes, and micronuclei and sister-chromatid exchanges in mouse bone marrow. The Ames/Salmonella assay, with and without S9 mix, did not show an increase in His+ revertants.

Published literature identified reduced testicular spermatozoids and reduced spermatogenesis in male mice dosed intraperitoneally for 7 days at doses equivalent to the human dose based on a mg/m^2 body surface area comparison.

16 HOW SUPPLIED/STORAGE AND HANDLING

How Supplied

20 mg tablet: white, round, biconvex tablets embossed "20" on one side.

NDC 82111-955-01: Bottle of 24, NDC 82111-955-02: Bottle of 100

Storage

Store at 20°C to 25°C (68°F to 77°F) excursions permitted 15°C to 30°C (59°F to 86°F) [see USP Controlled Room Temperature].

Dispense in a tight, light-resistant, child resistant container.

17 PATIENT COUNSELING INFORMATION

Discuss the following with patients prior to treatment with HEMADY:

Administration

- HEMADY is administered as part of combination regimens with anti-myeloma products; instruct patients to take HEMADY exactly as prescribed in the Prescribing Information of the anti-myeloma products administered with HEMADY [see Dosage and Administration (‎2.1) and Warning and Precautions (‎5.12)].

- Inform elderly patients regarding dose-reduction, if needed [see Dosage and Administration (‎2.2) and Use in Specific Populations (‎8.5)].

- Warn patients to not stop taking HEMADY abruptly or without first checking with their healthcare providers as there may be a need for gradual dose reduction to decrease the risk of adrenal insufficiency [see Warnings and Precautions (‎5.1)].

- HEMADY may be taken with or without food.

Alterations in Endocrine Function
Advise patients to inform any medical attendants that they are taking corticosteroids, as prolonged use may cause adrenal insufficiency, Cushing's syndrome and make patients dependent on corticosteroids. Instruct patients to notify their healthcare provider if they have diabetes, or thyroid gland problems as the dose of medications used to control these other conditions may need to be adjusted while they are taking HEMADY [see Warnings and Precautions (‎5.1)].
Advise the patient that, following prolonged therapy, withdrawal of corticosteroids may result in symptoms of the corticosteroid withdrawal syndrome including myalgia, arthralgia, and malaise. Advise patients to not discontinue use of HEMADY abruptly or without medical supervision [see Warnings and Precautions (‎5.1)].
Immunosuppression and Increased Risk of Infection
Advise patients that they are at increased risk of infection. Tell patients to inform their healthcare provider if they have had recent or ongoing infections or if they have recently received a vaccine. Medical advice should be sought immediately if the patient develops fever or other signs of infection. Patients should be made aware that some infections can potentially be severe and fatal [see Warnings and Precautions (‎5.2)].
Warn patients who are on corticosteroids to avoid exposure to chickenpox or measles and to alert their healthcare provider immediately if they are exposed [see Warnings and Precautions (‎5.2)].

Alterations in Cardiovascular/Renal Function
Inform patients that HEMADY can cause an increase in blood pressure and water retention. If this occurs, dietary salt restriction and potassium supplementation may be needed [see Warnings and Precautions (‎5.3)].
Venous and Arterial Thromboembolism
Inform patients of the potential risk of developing venous and arterial thromboembolism and discuss the need for appropriate prophylactic treatment [see Warnings and Precautions (‎5.4)].
Vaccination
Inform patients that they may receive concurrent vaccinations with use of HEMADY, except for live-attenuated or live vaccines [see Warnings and Precautions (‎5.5)].
Ophthalmic Effects
Inform patients that HEMADY may cause cataracts or glaucoma and advise monitoring if corticosteroid therapy is continued for more than 6 weeks [see Warnings and Precautions (‎5.6)].
Gastrointestinal Perforation
HEMADY may increase the risk of developing gastrointestinal perforation. Advise patients to promptly seek medical attention if they develop unusually severe, persistent or worsening abdominal pain. Warn patients to avoid corticosteroids if there is a possibility of gastrointestinal perforation [see Warnings and Precautions (‎5.7)].
Osteoporosis
Advise patients about the risk of osteoporosis with prolonged use of HEMADY, which can predispose the patient to vertebral and long bone fractures [see Warnings and Precautions (‎5.8)].
Myopathy
Advise patients to contact their healthcare provider if they experience new or worsening symptoms of myopathy such as unexplained muscle pain, tenderness or weakness [see Warnings and Precautions (‎5.9)].
Behavioral and Mood Disturbances
Advise patients about the potential for severe behavioral and mood changes with HEMADY and encourage them to seek medical attention if psychiatric symptoms develop [see Warnings and Precautions (‎5.10)].
Kaposi’s Sarcoma
Advise patients about the risk of Kaposi’s sarcoma in patients receiving corticosteroid therapy. Advise patients to discontinue HEMADY in case Kaposi’s sarcoma is diagnosed [see Warnings and Precautions (‎5.11)].
HEMADY in Combination with Anti-Myeloma Products
Advise patients about the risk of adverse reactions which may occur when HEMADY is taken in combination with anti-myeloma products. Inform patients of the possible adverse reactions that could occur with the prescribed combination regimen, as detailed in the Prescribing Information of these products [see Warnings and Precautions (‎5.12)].

Embryo-Fetal Toxicity
Advise females of reproductive potential of the potential risk to a fetus. Advise females to contact their healthcare provider if they become pregnant, or if pregnancy is suspected, during treatment with HEMADY [see Warnings and Precautions (‎5.13) and Use in Specific Populations (‎8.1)].
Drug Interactions
Certain medications can cause an interaction with HEMADY. Advise patients to inform their healthcare provider of all the medicines the patient is taking, including over-the-counter medicines, dietary supplements, and herbal products. Inform patients that alternate therapy, dosage adjustment, and/or special test(s) may be needed during the treatment [see Drug Interactions (‎7.1, ‎7.2)].
Females and Males of Reproductive Potential
Advise patients of reproductive potential to use effective contraception during treatment with HEMADY and for at least one month after the last dose [see Use in Specific Populations (‎8.3)].
Lactation
Advise women not to breastfeed during treatment with HEMADY and for 2 weeks after the last dose [see Use in Specific Populations (‎8.2)].

Manufactured for:
Dexcel Pharma Technologies Ltd
Nahum Haftzadi 21, Givat Shaul
Jerusalem, Israel 9548402
Distributed by:
Edenbridge Pharmaceuticals, LLC
Parsippany, NJ 07054